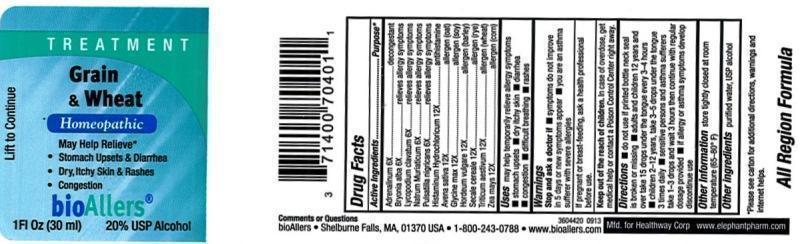 DRUG LABEL: Grain and wheat
NDC: 57955-4127 | Form: LIQUID
Manufacturer: King Bio Inc.
Category: homeopathic | Type: HUMAN OTC DRUG LABEL
Date: 20150126

ACTIVE INGREDIENTS: EPINEPHRINE 6 [hp_X]/30 mL; BRYONIA ALBA ROOT 6 [hp_X]/30 mL; LYCOPODIUM CLAVATUM SPORE 6 [hp_X]/30 mL; SODIUM CHLORIDE 6 [hp_X]/30 mL; PULSATILLA PRATENSIS 6 [hp_X]/30 mL; HISTAMINE DIHYDROCHLORIDE 12 [hp_X]/30 mL; AVENA SATIVA POLLEN 12 [hp_X]/30 mL; SOYBEAN 12 [hp_X]/30 mL; HORDEUM VULGARE POLLEN 12 [hp_X]/30 mL; SECALE CEREALE POLLEN 12 [hp_X]/30 mL; TRITICUM AESTIVUM POLLEN 12 [hp_X]/30 mL; ZEA MAYS POLLEN 12 [hp_X]/30 mL
INACTIVE INGREDIENTS: ALCOHOL; WATER

Grain and Wheat

Drug Facts

________________________________________________________________________________________________

Active Ingredients: Adrenalinum 6X, Bryonia alba 6X, Lycopodium clavatum 6X, Natrum muriaticum 6X, Pulsatilla nigricans 6X, Histaminum hydrochloricum 12X, Avena sativa 12X, Glycine max 12X, Hordeum vulgare 12X, Secale cereale 12X, Triticum aestivum 12X, Zea mays 12X.

INDICATIONS AND USAGE

Uses may help temporarily relieve allergy symptoms •stomach upsets •dry itchy skin •diarrhea •congestion •difficult breathing •rashes

WARNINGS

Warnings: Stop and ask a doctor if •symptoms do not impove in 5 days or new symptoms appear •you are a asthma sufferer with severe allergies.

_______________________________________________________________________________________________________________

If pregnant or breast-feeding, ask a health professional before use.

Keep out of reach of children. In case of overdose, get medical help or contact a Poison Control Center right away.

DOSAGE AND ADMINISTRATION

Directions: •do not use if printed bottle neck seal is broken or missing •adults and children 12 years and over take 15 drops under the tongue every 3-4 hours 3 times daily •children 2-12 years, take 3-5 drops under the tongue 3 times daily •sensitive persons and asthma sufferers take 1-3 drops and wait 3 hours then continue with regular dosage provided •if allergy or asthma symptoms develop discontinue use.

Other Information: store tightly closed at room temperature (65-80°F).

INACTIVE INGREDIENT

Other ingredients: purified water, USP alcohol.

Drug Facts

________________________________________________________________________________________________

Active Ingredients Purpose

Adrenalinum 6X.......................................................decongestant

Bryonia alba 6X......................................relieves allergy symptoms

Lycopodium clavatum 6X.........................relieves allergy symptoms

Natrum muriaticum 6X............................relieves allergy symptoms

Pulsatilla nigricans 6X..............................relieves allergy symptoms

Histaminum hydrochloricum 12X................................antihistamine

Avena sativa 12X......................................................allergen (oat)

Glycine max 12X......................................................allergen (soy)

Hordeum vulgare 12X............................................allergen (barley)

Secale cereale 12X....................................................allergen (rye)

Triticum aestivum 12X...........................................allergen (wheat)

Zea mays 12X..........................................................allergen(corn)